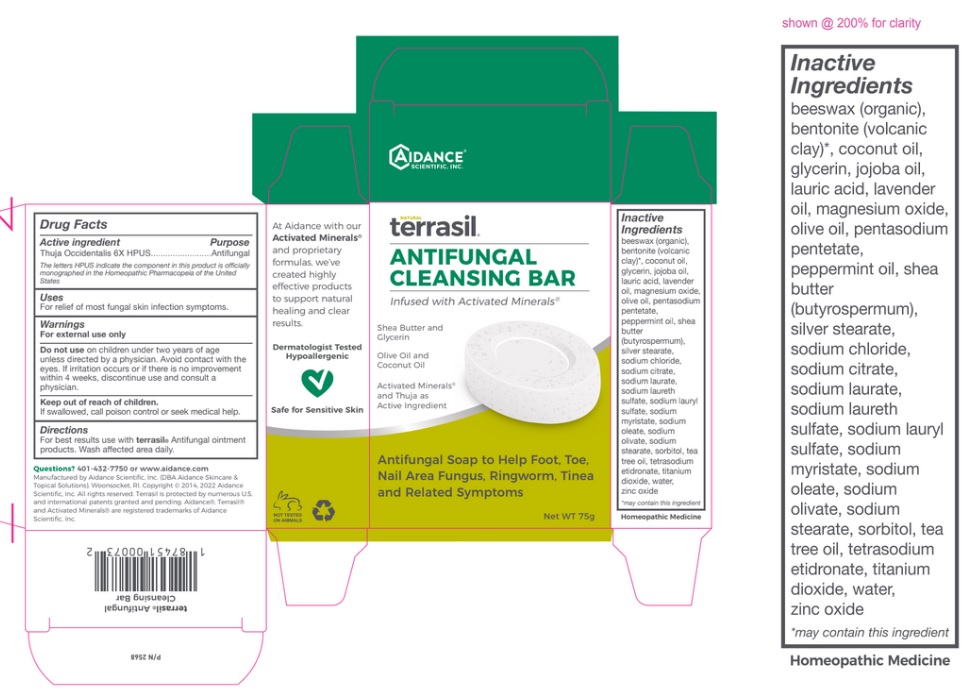 DRUG LABEL: Terrasil Antifungal Cleansing Bar
NDC: 24909-217 | Form: SOAP
Manufacturer: Aidance Skincare & Topical Solutions, LLC
Category: homeopathic | Type: HUMAN OTC DRUG LABEL
Date: 20220527

ACTIVE INGREDIENTS: THUJA OCCIDENTALIS WHOLE 6 [hp_X]/1 g
INACTIVE INGREDIENTS: YELLOW WAX; BENTONITE; COCONUT OIL; JOJOBA OIL; GLYCERIN; LAURIC ACID; LAVENDER OIL; MAGNESIUM OXIDE; OLIVE OIL; PENTASODIUM PENTETATE; PEPPERMINT OIL; SHEA BUTTER; SODIUM CHLORIDE; SODIUM CITRATE; SODIUM LAURATE; SODIUM LAURETH SULFATE; SODIUM LAURYL SULFATE; SODIUM MYRISTATE; SODIUM OLEATE; SODIUM OLIVATE; SODIUM STEARATE; SORBITOL; TEA TREE OIL; ETIDRONATE TETRASODIUM; TITANIUM DIOXIDE; WATER; ZINC OXIDE; SILVER OXIDE; STEARIC ACID

Drug Facts

Active Ingredient and Purpose

Thuja Occidentalis 6X HPUS as an Antifungal

The letters HPUS indicate the component(s) in this product is (are) officially monographed in the Homeopathic Pharmacopeia of the United States

Uses

For relief of most fungal skin infection symptoms

Warnings

For external use only
Do not use on children under two years of age unless directed by a physician. Avoid contact with the eyes. If irritation occurs or if there is no improvement within 4 weeks, discontinue use and consult a physician.
Keep out of reach of children.
If swallowed, call poison control or seek medical help

Directions

For best results use with terrasil® Antifungal ointment products. Wash affected area daily.

Inactive Ingredients

beeswax (organic), bentonite (volcanic clay)*, coconut oil, glycerin, jojoba oil, lauric acid, lavender oil, magnesium oxide, olive oil, pentasodium pentetate, peppermint oil, shea butter (butyrospermum), silver stearate, sodium chloride, sodium citrate, sodium laurate, sodium laureth sulfate, sodium lauryl sulfate, sodium myristate, sodium oleate, sodium olivate, sodium stearate, sorbitol, tea tree oil, tetrasodium etidronate, titanium dioxide, water, zinc oxide *may contain this ingredient

Questions?

401-432-7750 or www.aidance.com